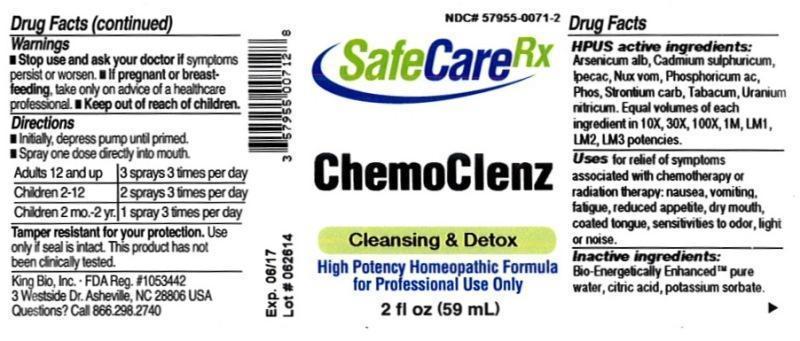 DRUG LABEL: ChemoClenz
NDC: 57955-0071 | Form: LIQUID
Manufacturer: King Bio Inc.
Category: homeopathic | Type: HUMAN OTC DRUG LABEL
Date: 20150309

ACTIVE INGREDIENTS: ARSENIC TRIOXIDE 10 [hp_X]/59 mL; CADMIUM SULFATE 10 [hp_X]/59 mL; IPECAC 10 [hp_X]/59 mL; STRYCHNOS NUX-VOMICA SEED 10 [hp_X]/59 mL; PHOSPHORIC ACID 10 [hp_X]/59 mL; PHOSPHORUS 10 [hp_X]/59 mL; STRONTIUM CARBONATE 10 [hp_X]/59 mL; TOBACCO LEAF 10 [hp_X]/59 mL; URANYL NITRATE HEXAHYDRATE 10 [hp_X]/59 mL
INACTIVE INGREDIENTS: WATER; ANHYDROUS CITRIC ACID; POTASSIUM SORBATE

ChemoClenz

ACTIVE INGREDIENT

Drug Facts__________________________________________________________________________________________________________

HPUS active ingredients: Arsenicum album, Cadmium sulphuricum, Ipecacuanha, Nux vomica, Phosphoricum acidum, Phosphorus, Strontium carbonicum, Tabacum, Uranium nitricum. Equal volumes of each ingredient in 10X, 30X, 100X, 1M, LM1, LM2, LM3 potencies.

INDICATIONS AND USAGE

Uses for relief of symptoms associated with chemotherapy or radiation therapy: nausea, vomiting, fatigue, reduced appetite, dry mouth, coated tongue, sensitivities to odor, light or noise.

Inactive Ingredients:

Bio-Energetically Enhanced™ pure water, citric acid and potassium sorbate.

Warnings

- Stop use and ask your doctor if symptoms persist or worsen.
- If pregnant or breast-feeding, take only on advice of a healthcare professional.

- Keep out of reach of children.

Directions

- Initially, depress pump until primed.
- Spray one dose directly into mouth.
- Adults 12 and up: 3 sprays 3 times per day.
- Children 2-12 years: 2 sprays 3 times per day.
- Children 2 mo-2 yr: 1 spray 3 times per day.

OTHER SAFETY INFORMATION

Tamper resistant for your protection. Use only if safety seal is intact. This product has not been clinically tested.

PURPOSE

Uses for relief of symptoms associated with chemotherapy or radiation therapy:

- nausea
- vomiting
- fatigue
- reduced appetite
- dry mouth
- coated tongue
- sensitivities to odor
- light or noise